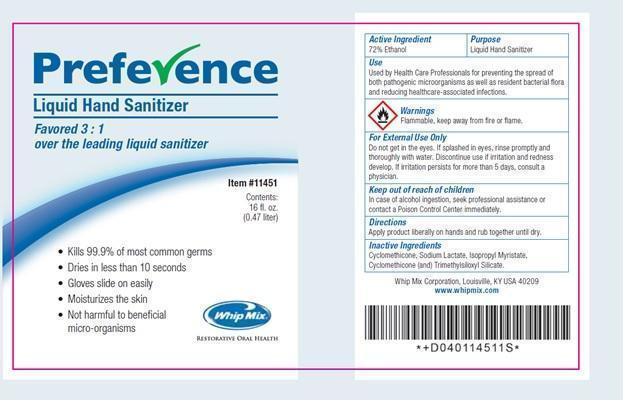 DRUG LABEL: Preference Hand Sanitizer
NDC: 62223-001 | Form: SPRAY
Manufacturer: Whip Mix Corporation
Category: otc | Type: HUMAN OTC DRUG LABEL
Date: 20200318

ACTIVE INGREDIENTS: ALCOHOL 340.56 mL/470 mL
INACTIVE INGREDIENTS: CYCLOMETHICONE; SODIUM LACTATE; ISOPROPYL MYRISTATE

Preference Hand Sanitizer

Active Ingredient

Ethanol 72%

Purpose

Liquid Hand Sanitizer

Use

Used by Health Care Professionals for preventing the spread of both pathogenic microorganisms as well as resident bacterial flora and reducing healthcare-associated infections.

Warnings

Flammable, Keep away from fire or flame.

For External Use Only

Do not get in the eyes. If splashed in eyes, rinse promptly and thoroughy with water. Discontinue use if irritation and redness develop. If irritation persists for more that 5 days, consult a physician.

Keep out of reach of children

In case of alcohol ingestion, seek professional assistance or contact a Poison Control Center immediately.

Directions

Apply product liberally on hands and rub together until dry.

Inactive Ingredients

Cyclomethicone, Sodium Lactate, Isopropyl Myristace, Cyclomethicone (and) Trimethyisiloxyl Silicane.

Principal Display Panel

Preference

Liquid Hand Sanitizer

Favored 3:1

over the leanding liquid sanitizer

- Kills 99.9% of most common germs
- Dries in less than 10 seconds
- Moisturizes the skin
- Not harmful to beneficial micro-organisms